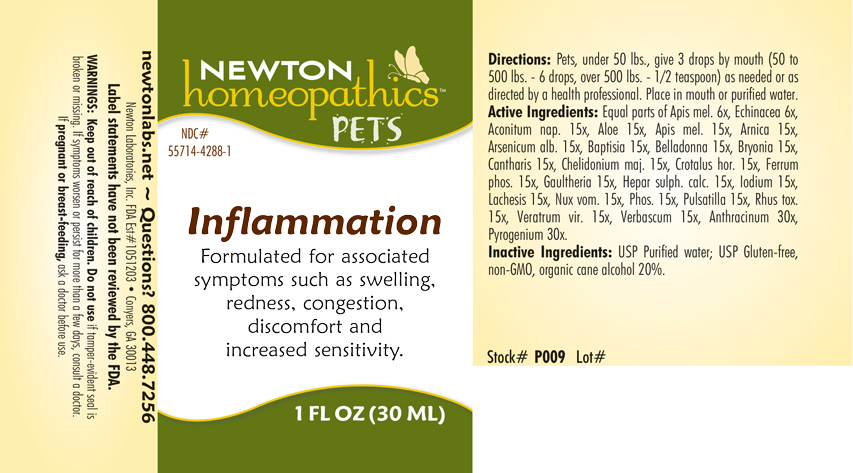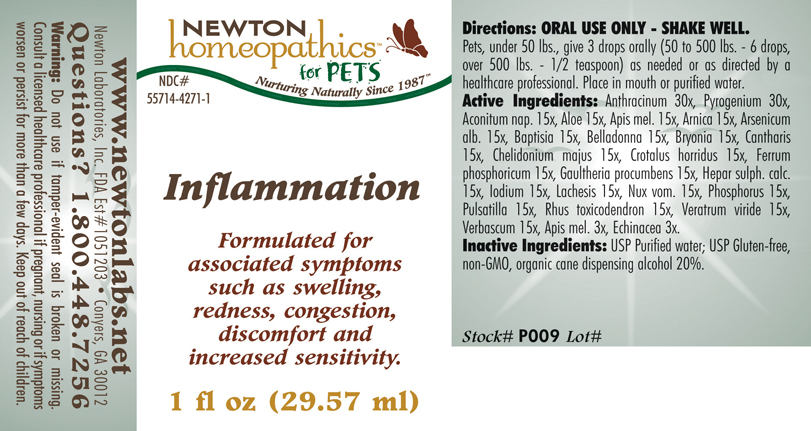 DRUG LABEL: Inflammation
NDC: 55714-4271 | Form: LIQUID
Manufacturer: Newton Laboratories, Inc.
Category: homeopathic | Type: OTC ANIMAL DRUG LABEL
Date: 20190114

ACTIVE INGREDIENTS: Bacillus Anthracis Immunoserum Rabbit 30 [hp_X]/1 mL; Rancid Beef 30 [hp_X]/1 mL; Aconitum Napellus 15 [hp_X]/1 mL; Aloe 15 [hp_X]/1 mL; Apis Mellifera 15 [hp_X]/1 mL; Arnica Montana 15 [hp_X]/1 mL; Arsenic Trioxide 15 [hp_X]/1 mL; Baptisia Tinctoria Root 15 [hp_X]/1 mL; Atropa Belladonna 15 [hp_X]/1 mL; Bryonia Alba Root 15 [hp_X]/1 mL; Lytta Vesicatoria 15 [hp_X]/1 mL; Chelidonium Majus 15 [hp_X]/1 mL; Crotalus Horridus Horridus Venom 15 [hp_X]/1 mL; Ferrosoferric Phosphate 15 [hp_X]/1 mL; Gaultheria Procumbens Top 15 [hp_X]/1 mL; Calcium Sulfide 15 [hp_X]/1 mL; Iodine 15 [hp_X]/1 mL; Lachesis Muta Venom 15 [hp_X]/1 mL; Strychnos Nux-vomica Seed 15 [hp_X]/1 mL; Phosphorus 15 [hp_X]/1 mL; Pulsatilla Vulgaris 15 [hp_X]/1 mL; Toxicodendron Pubescens Leaf 15 [hp_X]/1 mL; Veratrum Viride Root 15 [hp_X]/1 mL; Verbascum Thapsus 15 [hp_X]/1 mL; Echinacea, Unspecified 3 [hp_X]/1 mL
INACTIVE INGREDIENTS: Alcohol

Inflammation

PRODUCT NAME & INDICATIONS SECTION

Inflammation Formulated for associated symptoms such as swelling, redness, congestion, discomfort and increased sensitivity.

DIRECTIONS SECTION

Pets, under 50 lbs., give 3 drops by mouth (50 to 500 lbs. - 6 drops, over 500 lbs. - 1/2 teaspoon) as needed or as directed by a health professional. Place in mouth or purified water.

ACTIVE INGREDIENT SECTION

Equal parts of Apis mel. 6x, Echinacea 6x, Aconitum nap. 15x, Aloe 15x, Apis mel. 15x, Arnica 15x, Arsenicum alb. 15x, Baptisia 15x, Belladonna 15x, Bryonia 15x, Cantharis 15x, Chelidonium majus 15x, Crotalus horridus15x, Ferrum phosphoricum 15x, Gaultheria procumbens 15x, Hepar sulph. calc. 15x, Iodium 15x, Lachesis 15x, Nux vom. 15x, Phosphorus 15x, Pulsatilla 15x, Rhus toxicodendron 15x, Veratrum viride 15x, Verbascum 15x, Anthracinum 30x, Pyrogenium 30x.

INACTIVE INGREDIENT SECTION

USP Purified Water; USP Gluten-free, non-GMO, organic cane alcohol 20%.

QUESTIONS SECTION

newtonlabs.net Questions? 1.800.448.7256
Newton Laboratories, Inc. FDA Est # 1051203 - Conyers, GA 30013

WARNINGS SECTION

WARNINGS: Keep out of reach of children. Do not use if tamper-evident seal is broken or missing. If symptoms worsen or persist for more than a few days, consult a doctor. If pregnant or breast-feeding, ask a doctor before use.

PREGNANCY OR BREAST FEEDING SECTION

If pregnant or breast-feeding, ask a doctor before use.

KEEP OUT OF REACH OF CHILDREN SECTION

Keep out of reach of children.